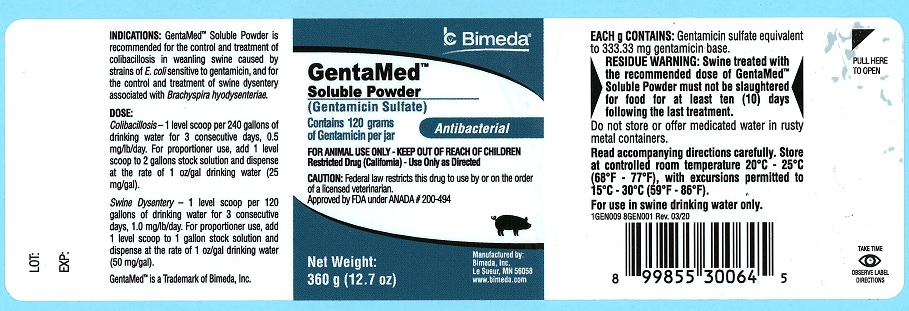 DRUG LABEL: GentaMed
NDC: 61133-5135 | Form: POWDER
Manufacturer: Bimeda, Inc.
Category: animal | Type: PRESCRIPTION ANIMAL DRUG LABEL
Date: 20220419

ACTIVE INGREDIENTS: gentamicin sulfate 120 g/360 g

DESCRIPTION

DESCRIPTION: Each gram of GentaMed™ Soluble Powder contains gentamicin sulfate equivalent to 333.33 mg gentamicin base.

RESIDUE WARNING

RESIDUE WARNING: For use in swine drinking water only. Swine treated with the recommended dose of GentaMed™ Soluble Powder must not be slaughtered for food for at least ten (10) days following the last treatment.

INDICATIONS AND USAGE

INDICATIONS: GentaMed™ Soluble Powder is recommended for the control and treatment of colibacillosis in weanling swine caused by strains of E. coli sensitive to gentamicin and for the control and treatment of swine dysentery associated with Brachyspira hyodysenteriae.

DOSAGE AND ADMINISTRATION:

GentaMed Soluble Powder is available in a 360 gram jar. The 360 gram jar contains a scoop that provides approximately 18 grams of product when level full.

For Control and treatment of Colibacillosis-Administer GentaMed Soluble Powder in drinking water at the recommended level of 25 mg per gallon (1 scoop/240 gallons) for three consecutive days.

For Control and treatment of Swine Dysentery-Administer GentaMed Soluble Powder in drinking water at the recommended level of 50 mg per gallon (1 scoop/120 gallons) for three consecutive days.

The concentration of the medication should be adjusted in extremely hot or cold weather to ensure a gentamicin dosage of approximately 0.5 mg/lb/day for 3 days for colibacillosis or 1.0 mg/lb/day for 3 days for swine dysentery. A 50-lb pig will, under average conditions, consume 0.9 gallons of water per day.

For swine dysentery, if the condition recurs, the medication may be repeated. Because of the tendency for the disease to recur on a premise with a history of swine dysentery, a control program should be used following treatment.

DIRECTIONS FOR USE:

To prepare medicated water, mix GentaMed Soluble Powder and drinking water according to the following tables:

Proportioner Use:

For Control and Treatment of Colibacillosis

Add 18 g (1 scoop) GentaMed Soluble Powder to 2 gallons of water to make stock solution and dispense at the rate of one ounce per gallon of drinking water. This will result in drinking water that contains 25 mg/gallon.

For Control and Treatment of Swine Dysentery

Add 18 g (1 scoop) GentaMed Soluble Powder to 1 gallon of water to make stock solution and dispense at the rate of one ounce per gallon of drinking water. This will result in drinking water that contains 50 mg/gallon.

Bulk Preparation:

For Control and Treatment of Colibacillosis

Add 18 g (1 scoop) GentaMed Soluble Powder to 240 gallons of water.

For Control and Treatment of Swine Dysentery

Add 18 g (1 scoop) GentaMed Soluble powder to 120 gallons of water.

Medicated drinking water should not be stored or offered in rusty containers since the drug is quickly destroyed in such containers.

Medicated water should be prepared daily and be the sole source of drinking water for 3 consecutive days.

The daily water consumption figures shown below are approximations for mild temperatures and are presented as a guide only. Actual water consumption varies with environmental temperature, humidity, and diet.

Approximate Daily Water Consumption

Weight of Pig(lb) | Gallon for 5 Pigs | Gallons for 10 Pigs
25 | 3.0 | 6.0
50 | 4.5 | 9.0
75 | 6.0 | 12.0
100 | 7.5 | 15.0

ADVERSE REACTIONS

SIDE EFFECTS: There have been no reported side effects following the recommended use of GentaMed™ Soluble Powder in swine.

CONTRAINDICATIONS

CONTRAINDICATIONS: There are no known contraindications to this drug when used as directed.

To report suspected adverse drug events, for technical assistance or to obtain a copy of the Safety Data Sheet (SDS), contact Bimeda, Inc. at 1-888-524-6332. For additional information about adverse drug experience reporting for animal drugs, contact FDA at 1-888-FDA-VETS or online at www.fda.gov/reportanimalae.

PRECAUTIONS

PRECAUTIONS: Store at controlled room temperature 20°C - 25°C (68°F - 77°F), with excursions permitted to 15°C - 30°C (59°F - 86°F).

HOW SUPPLIED

HOW SUPPLIED: GentaMed™ Soluble Powder is available in a 360 gram jar with 12 jars per shipper.

DESCRIPTION

GentaMed™ Soluble Powder

(Gentamicin Sulfate)

Contains 120 grams of Gentamicin per jar

Antibacterial

FOR ANIMAL USE ONLY - KEEP OUT OF REACH OF CHILDREN

Restricted Drug (California)-Use Only as Directed

CAUTION: Federal law restricts this drug to use by or on the order of a licensed veterinarian.

Approved by FDA under ANADA # 200-494

Net weight: 360 g (12.7 oz)